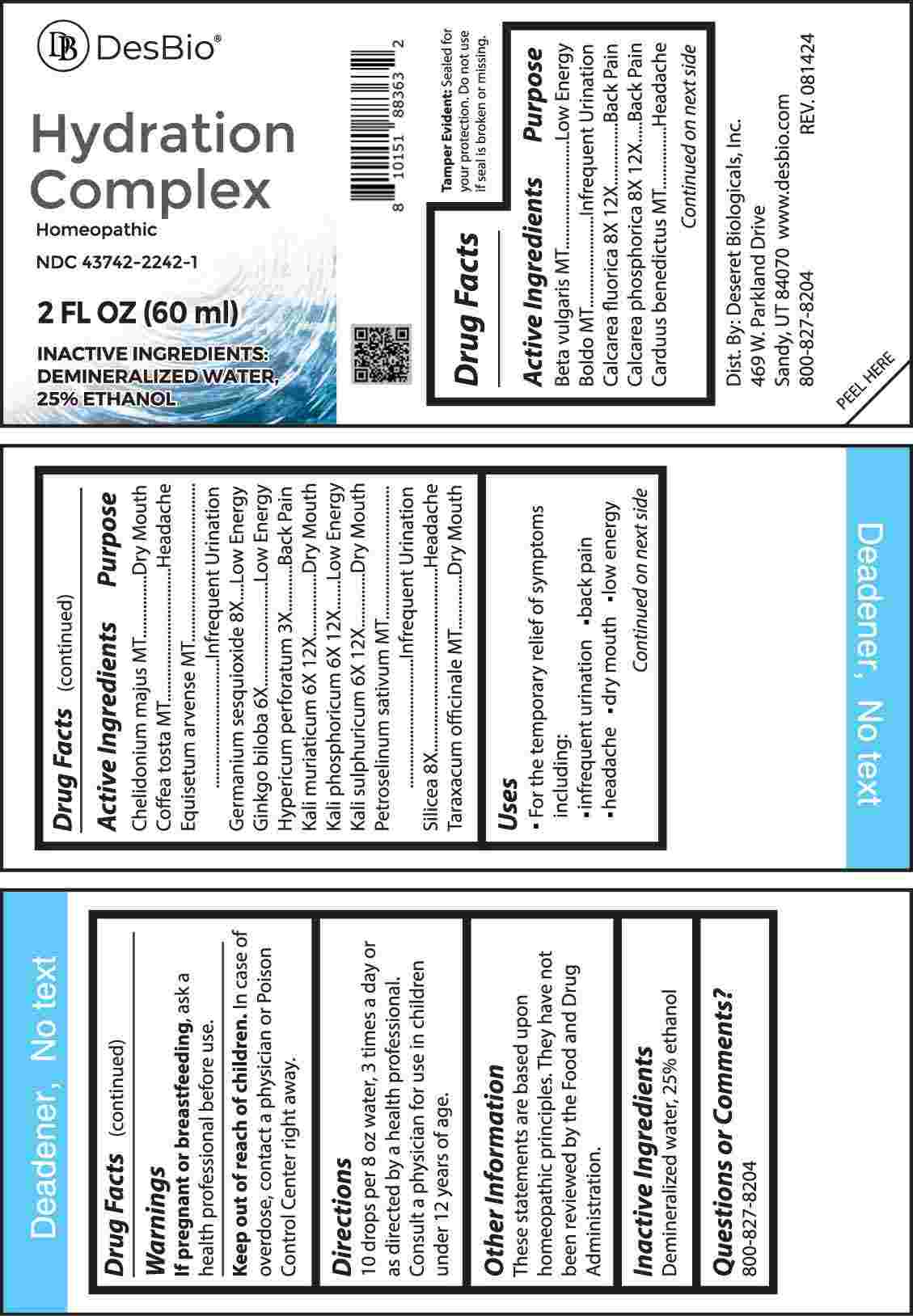 DRUG LABEL: Hydration Complex
NDC: 43742-2242 | Form: LIQUID
Manufacturer: Deseret Biologicals, Inc.
Category: homeopathic | Type: HUMAN OTC DRUG LABEL
Date: 20250116

ACTIVE INGREDIENTS: BETA VULGARIS WHOLE 1 [hp_X]/1 mL; PEUMUS BOLDUS LEAF 1 [hp_X]/1 mL; CALCIUM FLUORIDE 8 [hp_X]/1 mL; TRIBASIC CALCIUM PHOSPHATE 8 [hp_X]/1 mL; CENTAUREA BENEDICTA 1 [hp_X]/1 mL; CHELIDONIUM MAJUS WHOLE 1 [hp_X]/1 mL; COFFEA ARABICA SEED, ROASTED 1 [hp_X]/1 mL; EQUISETUM ARVENSE TOP 1 [hp_X]/1 mL; GERMANIUM SESQUIOXIDE 8 [hp_X]/1 mL; GINKGO 6 [hp_X]/1 mL; HYPERICUM PERFORATUM WHOLE 3 [hp_X]/1 mL; POTASSIUM CHLORIDE 6 [hp_X]/1 mL; DIBASIC POTASSIUM PHOSPHATE 6 [hp_X]/1 mL; POTASSIUM SULFATE 6 [hp_X]/1 mL; PETROSELINUM CRISPUM WHOLE 1 [hp_X]/1 mL; SILICON DIOXIDE 8 [hp_X]/1 mL; TARAXACUM OFFICINALE 1 [hp_X]/1 mL
INACTIVE INGREDIENTS: WATER; ALCOHOL

DRUG FACTS:

ACTIVE INGREDIENTS:

Beta Vulgaris MT, Boldo MT, Calcarea Fluorica 8X, 12X, Calcarea Phosphorica 8X, 12X, Carduus Benedictus MT, Chelidonium Majus MT, Coffea Tosta MT, Equisetum Arvense MT, Germanium Sesquioxide 8X, Ginkgo Biloba 6X, Hypericum Perforatum 3X, Kali Muriaticum 6X, 12X, Kali Phosphoricum 6X, 12X, Kali Sulphuricum 6X, 12X, Petroselinum Sativum MT, Silicea 8X, Taraxacum Officinale MT.

PURPOSE:

Beta Vulgaris – Low Energy, Boldo – Infrequent Urination, Calcarea Fluorica – Back Pain, Calcarea Phosphorica – Back Pain, Carduus Benedictus - Headache, Chelidonium Majus – Dry Mouth, Coffea Tosta - Headache, Equisetum Arvense – Infrequent Urination, Germanium Sesquioxide – Low Energy, Ginkgo Biloba – Low Energy, Hypericum Perforatum – Back Pain, Kali Muriaticum – Dry Mouth, Kali Phosphoricum – Low Energy, Kali Sulphuricum – Dry Mouth, Petroselinum Sativum – Infrequent Urination, Silicea - Headache, Taraxacum Officinale – Dry Mouth

USES:

• For the temporary relief of symptoms including:

• infrequent urination • back pain • headache • dry mouth • low energy

These statements are based upon homeopathic principles. They have not been reviewed by the Food and Drug Administration.

WARNINGS:

If pregnant or breastfeeding, ask a health professional before use.

Keep out of reach of children. In case of overdose, contact a physician or Poison Control Center right away.

Tamper Evident: Sealed for your protection. Do not use if seal is broken or missing.

KEEP OUT OF REACH OF CHILDREN:

In case of overdose, contact a physician or Poison Control Center right away.

DIRECTIONS:

10 drops per 8 oz water 3 times a day or as directed by a health professional. Consult a physician for use in children under 12 years of age.

INACTIVE INGREDIENTS:

Demineralized water, 25% ethanol

QUESTIONS:

Dist. By: Deseret Biologicals, Inc.

469 W. Parkland Drive

Sandy, UT 84070

www.desbio.com

800-827-8204

PACKAGE LABEL DISPLAY:

DesBio

Hydration Complex

Homeopathic

NDC 43742-2242-1

2 FL OZ (60 ml)